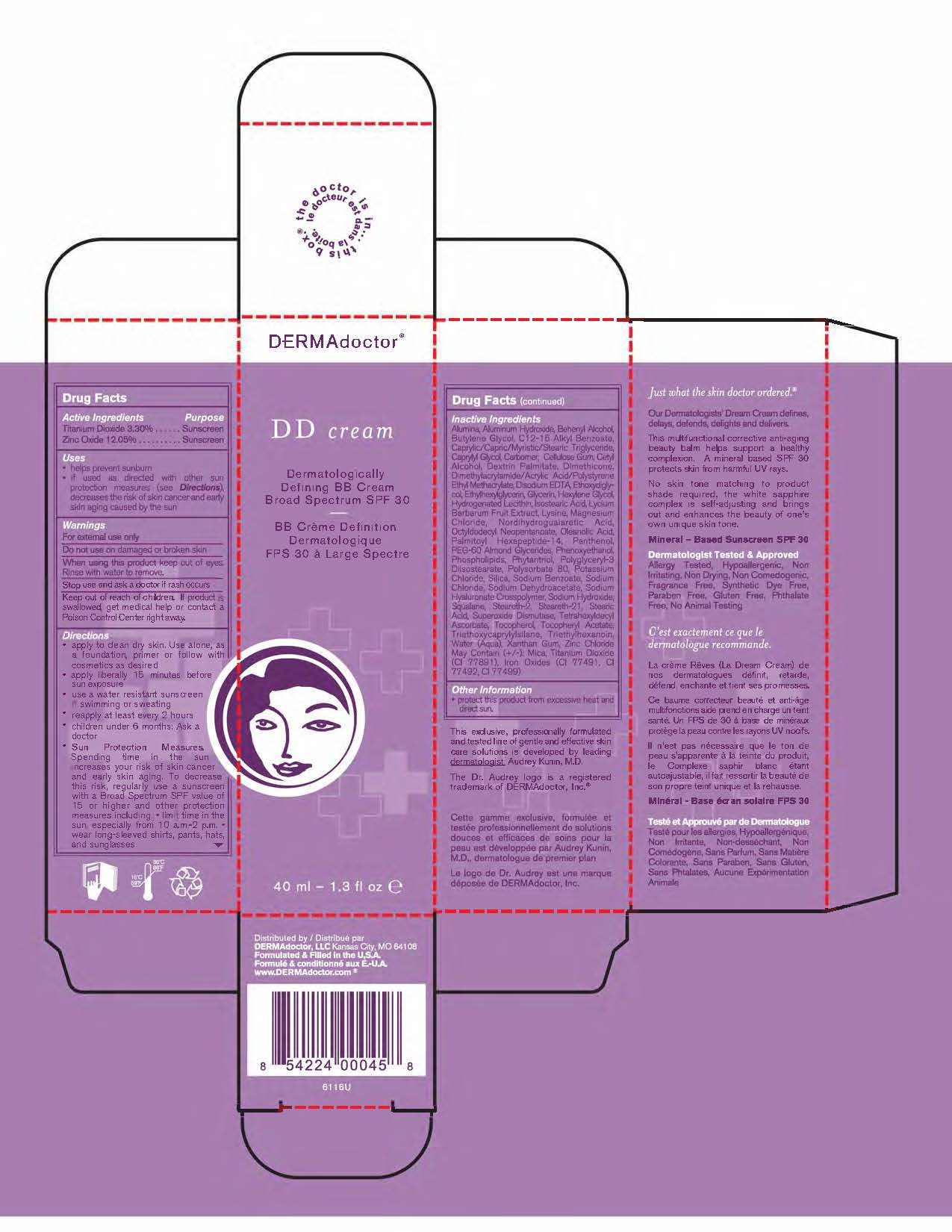 DRUG LABEL: DD Cream Dermatologically Defining BB Cream Broad Spectrum SPF 30
NDC: 59735-565 | Form: CREAM
Manufacturer: MANA Products, INC.
Category: otc | Type: HUMAN OTC DRUG LABEL
Date: 20240103

ACTIVE INGREDIENTS: TITANIUM DIOXIDE 3.3 g/100 g; ZINC OXIDE 12.05 g/100 g
INACTIVE INGREDIENTS: WATER; DEXTRIN PALMITATE (CORN; 20000 MW); 2,3-DIMETHYLACRYLIC ACID, (E)-; ETHOXYDIGLYCOL BEHENATE; HEXYLENE GLYCOL; LYSINE; NORDIHYDROGUAIARETIC ACID, (+/-)-; OCTYLDODECYL NEOPENTANOATE; PALMITOYL HEXAPEPTIDE-12; PHENOXYETHANOL; EGG PHOSPHOLIPIDS; POLYGLYCERYL-3 DISTEARATE; POLYSORBATE 80; POTASSIUM CHLORIDE; SILICON; SODIUM CHLORIDE; SQUALANE; STEARIC ACID; SUPEROXIDE DISMUTASE (CU-ZN) SACCHAROMYCES CEREVISIAE; TETRAHEXYLDECYL ASCORBATE; TRIETHYLHEXANOIN; XANTHAN GUM; BEHENYL BEHENATE; CAPRYLIC/CAPRIC/PALMITIC/STEARIC TRIGLYCERIDE; .ALPHA.-CELLULOSE; DISODIUM EDTA-COPPER; BUTYLENE GLYCOL; LYCIUM BARBARUM FRUIT; MAGNESIUM CHLORIDE; OLEANOLIC ACID; PANTHENOL; PEG-60 ALMOND GLYCERIDES; PHYTANTRIOL; DIMETHICONE; SODIUM BENZOATE; SODIUM DEHYDROACETATE; HYDROGENATED SOYBEAN LECITHIN; ISOSTEARIC ACID; STEARETH-2; STEARETH-21; TOCOPHEROL; TRIETHOXYCAPRYLYLSILANE; ALUMINUM; ALUMINUM HYDROXIDE; C12-15 ALCOHOLS; CAPRYLYL GLYCOL; CARBOMER 940; CETYL ALCOHOL

DD Cream SPF 30

ACTIVE INGREDIENTS

Titanium Dioxide 3.30%

Zinc Oxide 12.05%

USE

- Helps prevent sunburn.
- If used as directed with other sun protection measures (see Directions), decreases the risk of skin cancer and early skin aging caused by the sun.

WARNINGS

- For external use only
- Do not use on damaged or broken skin
- When using this product keep out of eyes. Rinse with water to remove.

DIRECTIONS

- Apply liberally 15 minutes before sun exposure
- Reapply at least every 2 hours
- Use water resistant sunscreen if swimming or sweathing
- Sun Protection Measures: Spending time in the sun decreases risk of skin cancer and early again. To decrease this risk, regulaory use a sunscreen with a Broad Spectrum SPF value of 15 or higher and other sun protection measures including: Limit time in the sun especially from 10:00 am - 2:00 pm. Wear long sleeved shirts, pants, hats and sunglasses.
- Children under 6 months: ask a doctor

INACTIVE INGREDIENTS

Alumina, Aluminum Hydroxide, Behenyl Alcohol, Butylene Glycol, C12-15 Alkyl Benzoate, Caprylic/Capric/Myristic/Stearic Triglyceride, Caprylyl Glycol, Carbomer, Cellulose Gum, Cety Alcohol, Dextrin Palmitate, Dimethicone, Dimethylacrylamide/Acrylic Acid/Plystyrene Ethyl Methacylate, Disodium EDTA, Ethoxydiglycol, Ethylhexylglycerin, Glycerin, Hexylene Glycol, Hydrogenated Lecithin, Isostearic Acid, Lycium Barbarum Fruit Extract, Lysine, Magnesium Chloride, Nordihydroguaiaretic Acid, Octyldodecyl Neopenanoate, Oleanolic Acid, Palmitoyl Hexapeptide-14, Panthenol, PEG-60 Almond Glycerides, Phenoxyethanol, Phospholipids, Phytantriol, Polygleceryl-3 Diisostearate, Polysorbate 80, Potassium Chloride, Silica, Sodium Benozate, Sodium Chloride, Sodium Dehydroacetate, Sodium Hyaluronate Crosspolymer, Sodium Hydroxide, Squalane, Steareth-2, Steareth-21, Stearic Acid, Superoxide Dismutase, Tetrahexyldecyl Ascorbate, Tocopherol, Tocopheryl Acetate, Triethoxycaprylylsilane, Triethylhexanoin, Water, Xanthan Gum, Zinc Chloride May Contain (+/-): Mica, Iron Oxides.

OTHER INFORMATION

- Protect this product form excessive heat and direct sun

Stop use and ask a doctor if rash occurs.

RECENT MAJOR CHANGES

Dosage & Admin update

Keep out of reach of children. If product is swallowed, get medical help or contact a Poison Control Center right away.